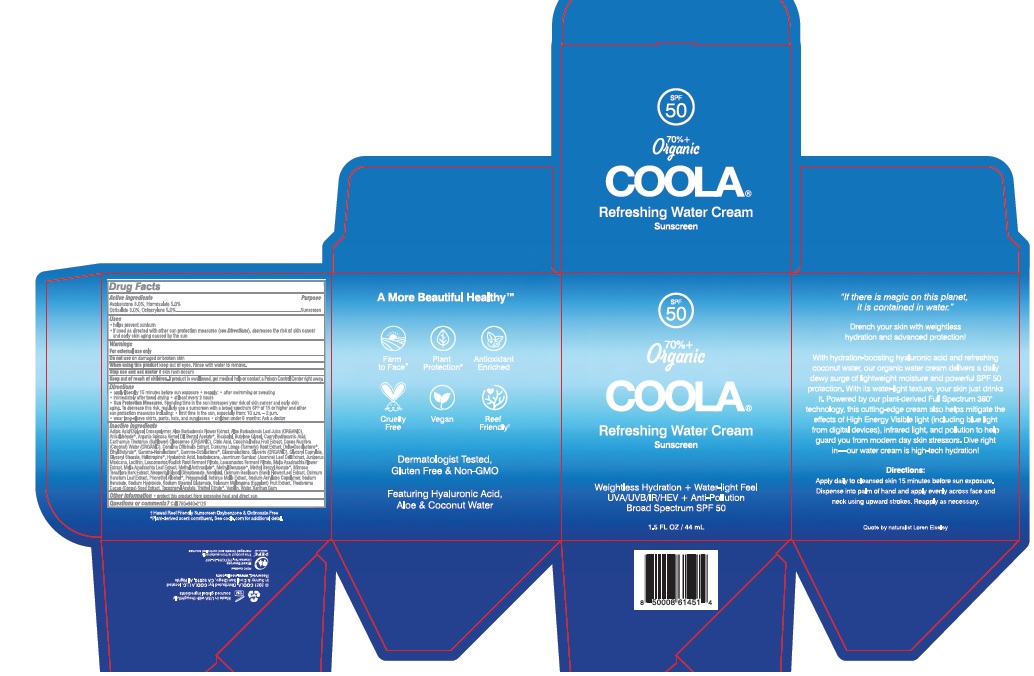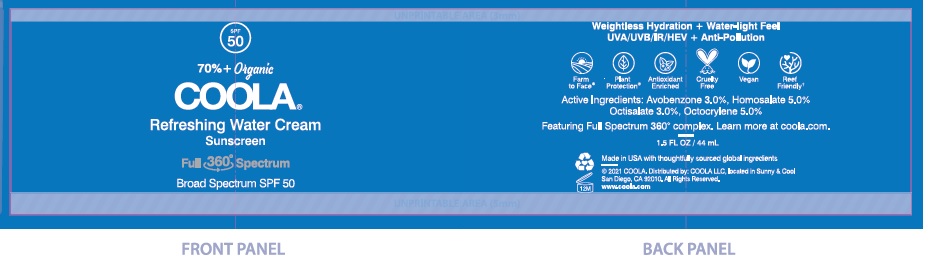 DRUG LABEL: COOLA Full Spectrum 360 Refreshing Water Cream SPF 50
NDC: 79753-020 | Form: CREAM
Manufacturer: COOLA LLC
Category: otc | Type: HUMAN OTC DRUG LABEL
Date: 20231220

ACTIVE INGREDIENTS: AVOBENZONE 3.0 g/100 mL; HOMOSALATE 5.0 g/100 mL; OCTISALATE 3.0 g/100 mL; OCTOCRYLENE 5.0 g/100 mL
INACTIVE INGREDIENTS: ADIPIC ACID/DIGLYCOL CROSSPOLYMER (20000 MPA.S); ALOE VERA FLOWER; ALOE VERA LEAF; P-ANISALDEHYDE; ARGAN OIL; BENZYL ACETATE; LEVOMENOL; BUTYLENE GLYCOL; CAPRYLHYDROXAMIC ACID; CARTHAMUS TINCTORIUS (SAFFLOWER) OLEOSOMES; CITRIC ACID MONOHYDRATE; COCCINIA GRANDIS LEAF; COCONUT WATER; CORALLINA OFFICINALIS; TURMERIC; .DELTA.-DECALACTONE; ETHYL BUTYRATE; .GAMMA.-NONALACTONE; .GAMMA.-OCTALACTONE; GLUCONOLACTONE; GLYCERIN; GLYCERYL CAPRYLATE; GLYCERYL MONOSTEARATE; PIPERONAL; HYALURONIC ACID; ISODODECANE; JASMINUM SAMBAC FLOWER; JUNIPERUS DEPPEANA WOOD OIL; LECITHIN, SOYBEAN; LEUCONOSTOC/RADISH ROOT FERMENT FILTRATE; AZADIRACHTA INDICA FLOWER; AZADIRACHTA INDICA LEAF; METHYL ANTHRANILATE; METHYL BENZOATE; METHYLBENZYL ACETATE; MIMOSA TENUIFLORA BARK; NEOPENTYL GLYCOL DIHEPTANOATE; NEROLIDOL; OCIMUM BASILICUM FLOWERING TOP; HOLY BASIL LEAF; PHENYLETHYL ALCOHOL; PROPANEDIOL; SCHINUS MOLLE FRUITING TOP; SODIUM ACRYLATE/STYRENE SULFONATE COPOLYMER (11000 MW); SODIUM BENZOATE; SODIUM HYDROXIDE; SODIUM STEAROYL GLUTAMATE; EGGPLANT; COCOA; .ALPHA.-TOCOPHEROL ACETATE; TRIETHYL CITRATE; VANILLIN; WATER; XANTHAN GUM

COOLA Full Spectrum 360 Refreshing Water Cream SPF 50

Drug Facts

Active Ingredients

Avobenzone 3.0%, Homosalate 5.0%, Octisalate 3.0%, Octocrylene 5.0%

Purpose

Suncreen

Uses

- helps prevent sunburn

• if used as directed with other sun protection measures (see Directions), decreases the risk of skin cancer

and early skin aging caused by the sun

Warnings

For external use only

Do not use on damaged or broken skin

When using this product keep out of eyes.Rinse with water to remove.

Stop use and ask doctor if skin rash occurs

Keep out of reach of children. If product is swallowed, get medical help or contact a Poison Control Center right away.

Directions
• apply liberally 15 minutes before sun exposure • reapply: ● after swimming or sweating
● immediately after towel drying ● at least every 2 hours
● Sun Protection Measures. Spending time in the sun increases your risk of skin cancer and early skin aging. To
decrease this risk, regularly use a sunscreen with a broad spection SPF of 15 or higher and other sun protection
measures including: ● limit time in the sun, especially from: 10 a.m. - 2 p.m.
● wear long-sleeve shirts, pants, hats, and sunglasses ●Children under 6 months: Ask a doctor

Inactive Ingredients
Adipic Acid/Diglycol Crosspolymer, Aloe Barbadensis Flower Extract, Aloe Barbadensis Leaf Juice, (ORGANIC)
Anisaldehyde*, Argania Spinosa Kernel Oil, Benzyl Acetate*, Bisabolol, Butylene Glycol, Caprylhydroxamic Acid,
Carthamus Tinctorius (Safflower) Oleosomes (ORGANIC), Citric Acid, Coccinia Indica Fruit Extract, Cocos Nucifera
(Coconut) Water (ORGANIC), Corallina Officinalis Extract, Curcuma Longa (Turmeric) Root Extract, Delta-Decalactone*,
Ethyl Butyrate*, Gamma-Nonalactone*, Gamma-Octalactone*, Gluconolactone, Glycerin (ORGANIC), Glyceryl Caprylate,
Glyceryl Stearate, Heliotropine*, Hyaluronic Acid, Isododecane, Jasminum Sambac (Jasmine) Leaf Cell Extract, Juniperus
Mexicana, Lecithin, Leuconostoc/Radish Root Ferment Filtrate, Leuconostoc Ferment Filtrate, Melia Azadirachta Flower
Extract, Melia Azadirachta Leaf Extract, Methyl Anthranilate*, Methyl Benzoate*, Methyl Benzyl Acetate*, Mimosa
Tenuiflora Bark Extract, Neopentyl Glycol Diheptanoate, Nerolidol, Ocimum Basilicum (Basil) Flower/Leaf Extract, Ocimum
Sanctum Leaf Extract, Phenethyl Alcohol*, Propanediol, Schinus Molle Extract, Sodium Acrylates Copolymer, Sodium
Benzoate, Sodium Hydroxide, Sodium Stearoyl Glutamate, Solanum Melongena (Eggplant) Fruit Extract, Theobroma
Cacao (Cocoa) Seed Extract, Tocopheryl Acetate, Triethyl Citrate*, Vanillin, Water, Xanthan Gum

Other information

- protect this product from excessive heat and direct sun

Questions or comments?
Call 760-940-2125

COOLA Label

SPF

50

70%+

Organic

COOLA®

Refreshing Water Cream

Sunscreen

1.5 FL OZ / 44 mL

Broad Spectrum SPF 70

Water Resistant (80 Minutes)

5.0 FL OZ / 148 mL

©2021 COOLA. Distributed by: COOLA LLC, located in

Sunny & Cool San Diego, CA 92010. All Rights Reserved.

†Hawaii Reef Friendly Sunscreen Oxybenzone & Octinoxate Free
*Plant-derived scent constituent. See coola.com for additional detail.

Carton

Bottle

res